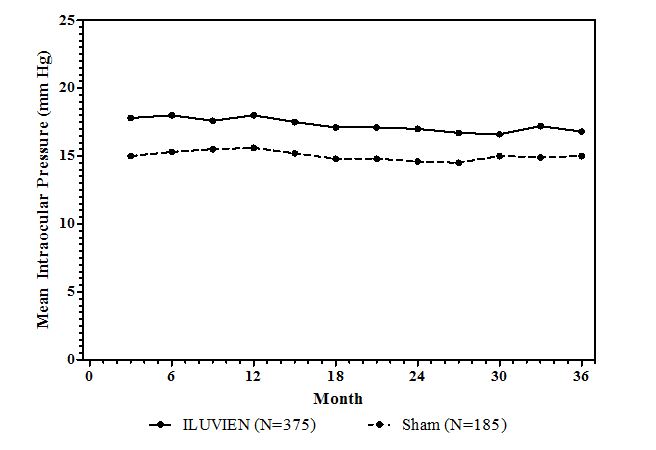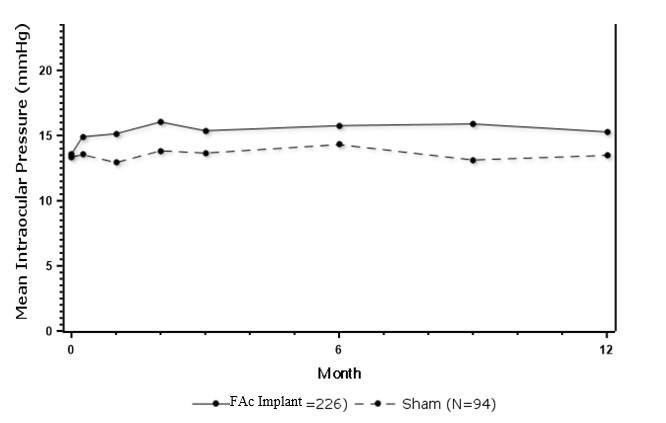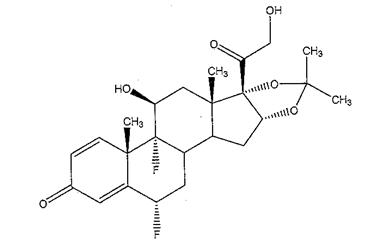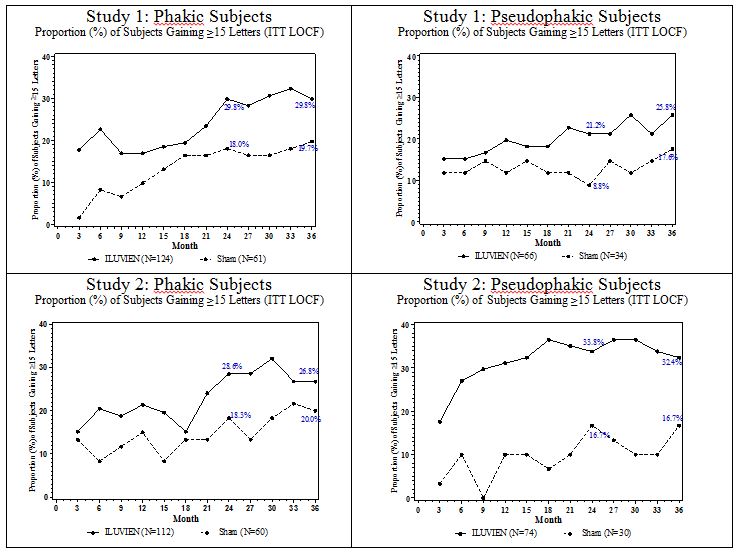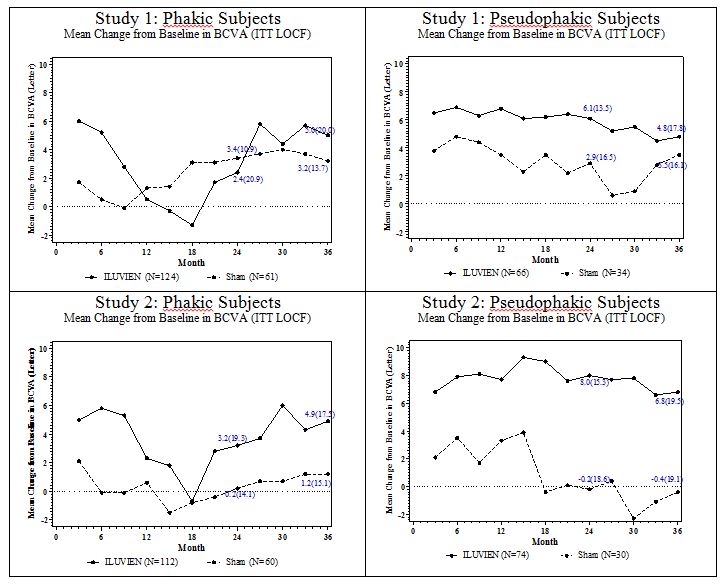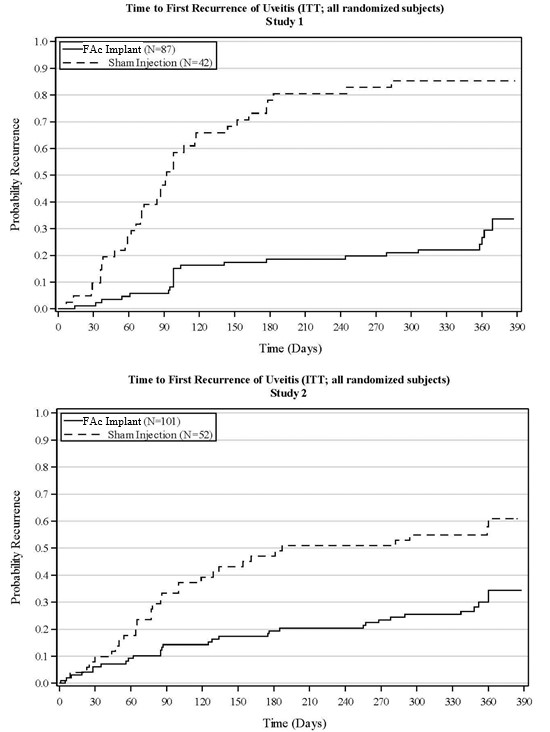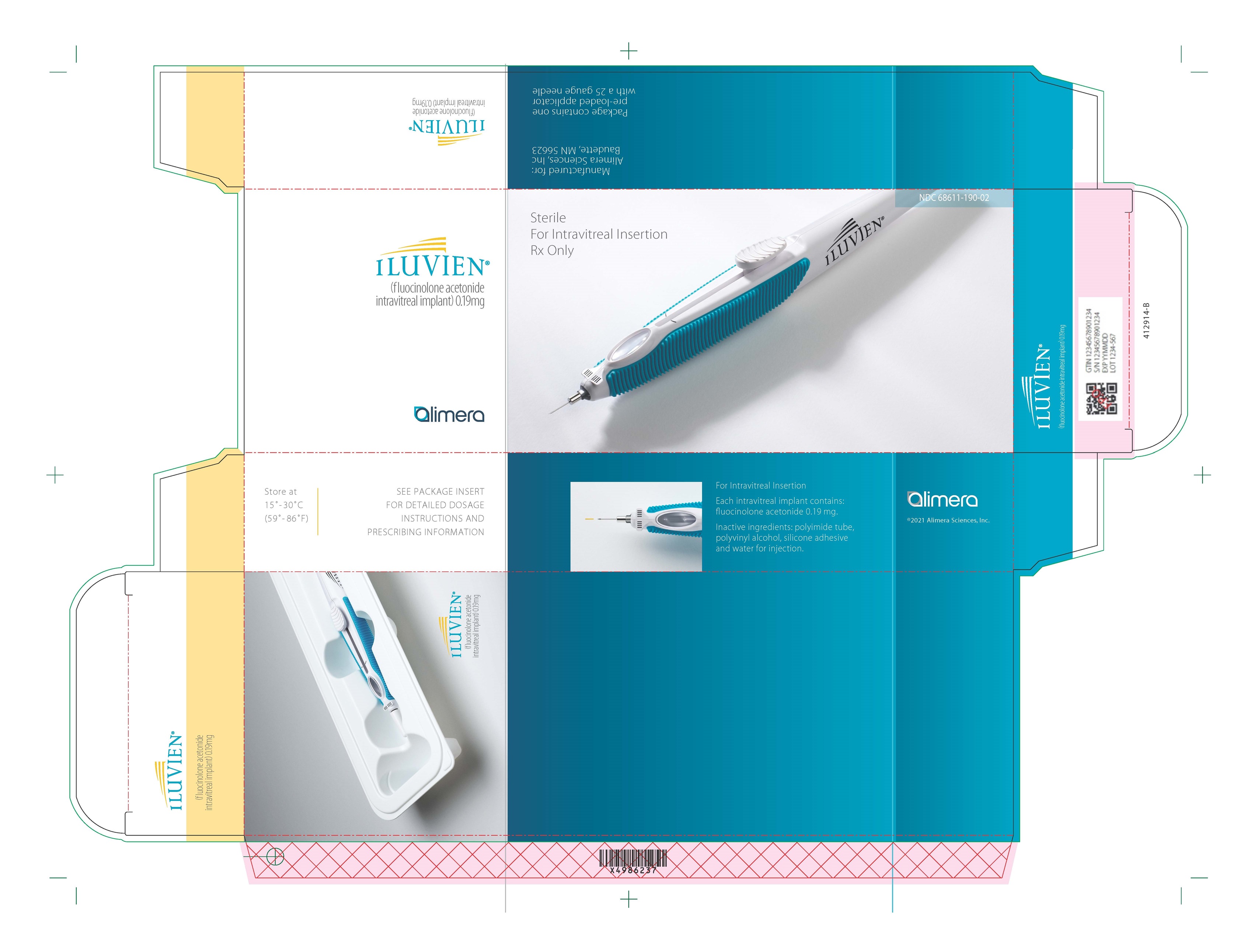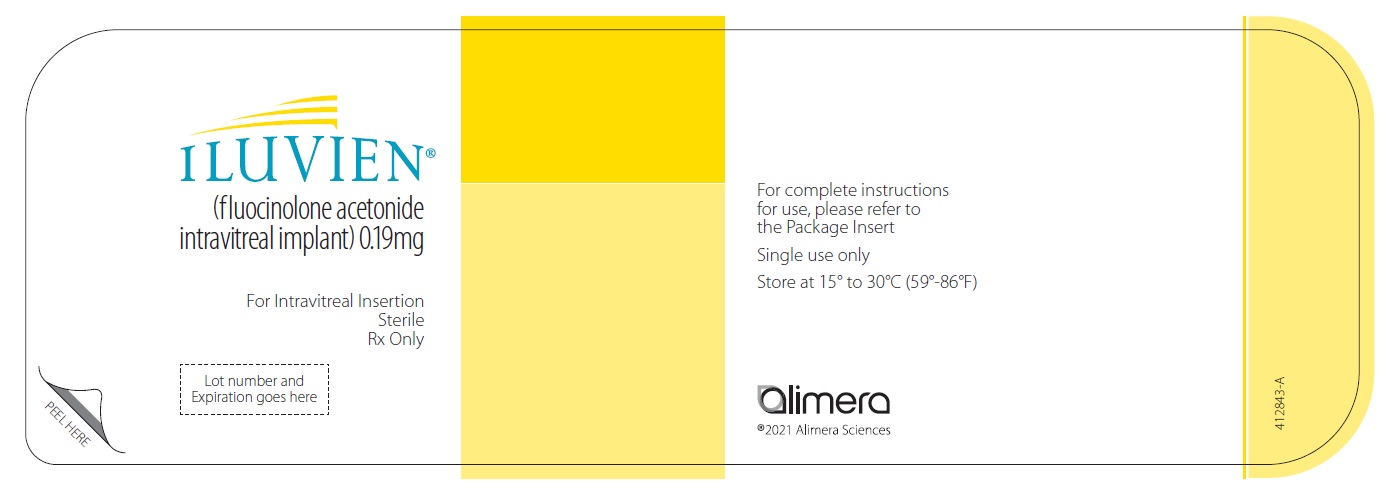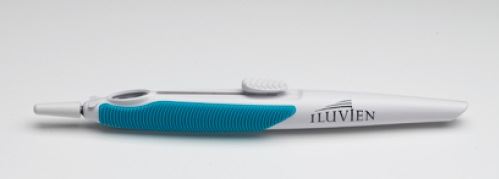 DRUG LABEL: Iluvien
NDC: 68611-190 | Form: IMPLANT
Manufacturer: ANI Pharmaceuticals, Inc.
Category: prescription | Type: HUMAN PRESCRIPTION DRUG LABEL
Date: 20260128

ACTIVE INGREDIENTS: FLUOCINOLONE ACETONIDE 0.19 mg/1 1
INACTIVE INGREDIENTS: POLYVINYL ALCOHOL; WATER

HIGHLIGHTS OF PRESCRIBING INFORMATION

These highlights do not include all the information needed to use ILUVIEN® safely and effectively. See full prescribing information for ILUVIEN.
ILUVIEN® (fluocinolone acetonide intravitreal implant),
0.19 mg, for intravitreal use
Initial U.S. Approval: 1963

RECENT MAJOR CHANGES

Indications and Usage, Chronic Non-Infectious Uveitis Affecting the Posterior Segment (1.2) 03/2025

1 INDICATIONS AND USAGE

ILUVIEN is a corticosteroid indicated for:

- the treatment of diabetic macular edema (DME) in patients who have been previously treated with a course of corticosteroids and did not have a clinically significant rise in intraocular pressure. (1.1)
- the treatment of chronic non-infectious uveitis affecting the posterior segment of the eye. (1.2)

2 DOSAGE AND ADMINISTRATION

- For ophthalmic intravitreal injection. (2.1)
- The intravitreal injection procedure should be carried out under aseptic conditions. (2.2)
- Following the intravitreal injection, patients should be monitored for elevation in intraocular pressure and for endophthalmitis. (2.2)

3 DOSAGE FORMS AND STRENGTHS

Intravitreal implant containing 0.19 mg fluocinolone acetonide in a drug delivery system. (3)

4 CONTRAINDICATIONS

- Ocular or Periocular Infections (4.1)
- Glaucoma (4.2)
- Hypersensitivity (4.3)

5 WARNINGS AND PRECAUTIONS

- Intravitreal injections have been associated with endophthalmitis, eye inflammation, increased intraocular pressure, and retinal detachments. Patients should be monitored following the injection. (5.1)
- Intraocular Pressure (IOP) Increase: Prolonged use of corticosteroids may result in glaucoma with damage to the optic nerve, defects in visual acuity, and fields of vision. (5.2)
- Cataracts: Use of corticosteroids may result in posterior subcapsular cataract formation. (5.3)
- Delayed Healing: The use of corticosteroids after cataract surgery may delay healing and increase the incidence of bleb formation. (5.4)
- Corneal and Scleral Melting: In those diseases causing thinning of the cornea or sclera, ophthalmic corticosteroids may lead to perforation of the globe. (5.5)
- Bacterial Infections: Prolonged use of corticosteroids may suppress the host response and thus increase the hazard of secondary ocular infections. In acute purulent conditions, steroids may mask infection or enhance existing infection. If signs and symptoms fail to improve after 2 days, the patient should be re-evaluated. (5.6)
- Viral Infections: Employment of a corticosteroid medication in the treatment of patients with a history of herpes simplex requires great caution. Use of ocular steroids may prolong the course and may exacerbate the severity of many viral infections of the eye (including herpes simplex). (5.7)
- Fungal Infections: Fungal infections of the cornea are particularly prone to develop coincidentally with long-term local corticosteroid application. Fungus invasion must be considered in any persistent corneal ulceration where a steroid has been used or is in use. (5.8)
- Implant Migration: The implant may migrate into the anterior chamber if the posterior lens capsule is not intact. (5.9)

6 ADVERSE REACTIONS

The most common adverse reactions reported are cataract development and increases in intraocular pressure. (6.1)

To report SUSPECTED ADVERSE REACTIONS, contact Alimera Sciences, Inc. at 1-844-445-8843 or FDA at 1-800-FDA-1088 or www.fda.gov/medwatch.

FULL PRESCRIBING INFORMATION

1 INDICATIONS AND USAGE

1.1 Diabetic Macular Edema

ILUVIEN® is indicated for the treatment of diabetic macular edema (DME) in patients who have been previously treated with a course of corticosteroids and did not have a clinically significant rise in intraocular pressure.

1.2 Chronic Non-Infectious Uveitis Affecting the Posterior Segment

ILUVIEN® is indicated for the treatment of chronic non-infectious uveitis affecting the posterior segment of the eye.

2 DOSAGE AND ADMINISTRATION

2.1 General Dosing Information

For ophthalmic intravitreal injection.

The initial prescription and renewal of the medication order of ILUVIEN should be made by a physician only after examination of the patient with the aid of magnification, such as slit lamp biomicroscopy, and, where appropriate, fluorescein staining.

2.2 Administration

The intravitreal injection procedure should be carried out under aseptic conditions, which include use of sterile gloves, a sterile drape, a sterile caliper, and a sterile eyelid speculum (or equivalent). Adequate anesthesia and a broad-spectrum microbicide should be given prior to the injection.

The injection procedure for ILUVIEN is as follows:

1. The exterior of the tray should not be considered sterile. An assistant (non-sterile) should remove the tray from the carton and examine the tray and lid for damage. If damaged, do not use unit.
  If acceptable, the assistant should peel the lid from the tray without touching the interior surface.
2. Visually check through the viewing window of the preloaded applicator to ensure that there is a drug implant inside.
3. Remove the applicator from the tray with sterile gloved hands touching only the sterile interior tray surface and applicator.
  Prior to injection, the applicator tip must be kept above the horizontal plane to ensure that the implant is properly positioned within the applicator.
4. To reduce the amount of air administered with the implant, the administration procedure requires two steps. Before inserting the needle into the eye, remove the protective cap then gently push the applicator button down and slide it to the first stop (at the curved black marks alongside the button track). At the first stop, release the button and it should move to the UP position. If the button does not rise to the UP position, do not proceed with this unit.
5. Optimal placement of the implant is inferior to the optic disc and posterior to the equator of the eye. Measure 4 millimeters inferotemporal from the limbus with the aid of calipers for point of entry into the sclera.
6. Inspect the tip of the needle to ensure it is not bent.
7. Gently displace the conjunctiva so that after withdrawing the needle, the conjunctival and scleral needle entry sites will not align. Care should be taken to avoid contact between the needle and the lid margin or lashes. Insert the needle through the conjunctiva and sclera. To release the implant, while the button is in the UP position, advance the button by sliding it forward to the end of the button track and remove the needle. Note: Ensure that the button reaches the end of the track before removing the needle.
8. Remove the lid speculum and perform indirect ophthalmoscopy to verify placement of the implant, adequate central retinal artery perfusion and absence of any other complications.

Following the injection, patients should be monitored for change in intraocular pressure and for endophthalmitis. Monitoring may consist of a check for perfusion of the optic nerve head immediately after the injection, tonometry within 30 minutes following the injection, and biomicroscopy between two and seven days following the injection. Patients should be instructed to report without delay any symptoms suggestive of endophthalmitis.

3 DOSAGE FORMS AND STRENGTHS

ILUVIEN is a non-bioerodable intravitreal implant in a drug delivery system containing 0.19 mg fluocinolone acetonide, designed to release fluocinolone acetonide at an initial rate of 0.25 mcg/day and lasting 36 months.

4 CONTRAINDICATIONS

4.1 Ocular or Periocular Infections

ILUVIEN is contraindicated in patients with active or suspected ocular or periocular infections including most viral disease of the cornea and conjunctiva including active epithelial herpes simplex keratitis (dendritic keratitis), vaccinia, varicella, mycobacterial infections and fungal diseases.

4.2 Glaucoma

ILUVIEN is contraindicated in patients with glaucoma, who have cup to disc ratios of greater than 0.8.

4.3 Hypersensitivity

ILUVIEN is contraindicated in patients with known hypersensitivity to any components of this product.

5 WARNINGS AND PRECAUTIONS

5.1 Intravitreal Injection-related Effects

Intravitreal injections, including those with ILUVIEN, have been associated with endophthalmitis, eye inflammation, increased or decreased intraocular pressure, and choroidal or retinal detachments. For patients with non-infectious uveitis affecting the posterior segment, hypotony has been observed within 24 hours of injection and has resolved within 2 weeks. Patients should be monitored following the intravitreal injection [see Patient Counseling Information (17)]. Patients may experience temporary blurred vision after injection of the implant.

5.2 Intraocular Pressure (IOP) Increase

Prolonged use of corticosteroids may result in the development of glaucoma with damage to the optic nerve, defects in visual acuity and fields of vision. Steroids should be used with caution in the presence of glaucoma. Intraocular pressure should be routinely monitored during the course of the treatment.

5.3 Cataracts

The use of corticosteroids may result in posterior subcapsular cataract formation.

5.4 Delayed Corneal Wound Healing

The use of corticosteroids after cataract surgery may delay healing and increase the incidence of bleb formation.

5.5 Corneal and Scleral Melting

Various ocular diseases and long-term use of topical corticosteroids have been known to cause corneal and scleral thinning. Use of ophthalmic corticosteroids in the presence of thin corneal or scleral tissue may lead to perforation of the globe.

5.6 Bacterial Infections

Prolonged use of corticosteroids may suppress the host immune response and thus increase the hazard of secondary ocular infections. Acute purulent or parasitic infections of the eye may be masked or activity enhanced by the presence of corticosteroid medication. If signs and symptoms fail to improve after 2 days, the patient should be reevaluated.

5.7 Viral Infections

Use of ocular corticosteroids may prolong the course and may exacerbate the severity of many viral infections of the eye (including herpes simplex). Employment of a corticosteroid medication in the treatment of patients with a history of herpes simplex requires great caution; frequent slit lamp microscopy is recommended.

5.8 Fungal Infections

Fungal infections of the cornea are particularly prone to develop coincidentally with long-term local corticosteroid application. Fungus invasion should be suspected in any persistent corneal ulceration where a corticosteroid has been used or is in use. Fungal cultures should be taken when appropriate.

5.9 Risk of Implant Migration

Patients in whom the posterior capsule of the lens is absent or has a tear are at risk of implant migration into the anterior chamber.

6 ADVERSE REACTIONS

6.1 Clinical Trials Experience

Because clinical trials are conducted under widely varying conditions, adverse reaction rates observed in the clinical trials of a drug cannot be directly compared to rates in the clinical trials of another drug and may not reflect the rates observed in practice.

Adverse reactions associated with ophthalmic steroids including ILUVIEN include cataract formation and subsequent cataract surgery, elevated intraocular pressure, which may be associated with optic nerve damage, visual acuity and field defects, secondary ocular infection from pathogens including herpes simplex, and perforation of the globe where there is thinning of the cornea or sclera.

Diabetic Macular Edema

ILUVIEN was studied in two multicenter, randomized, sham-controlled, double-masked trials in which patients with diabetic macular edema (DME) were treated with either ILUVIEN (n=375) or sham (n=185).

Table 1 summarizes safety data available when the last subject completed the last 36 month follow up visit for the two primary ILUVIEN trials. In these trials, subjects were eligible for retreatment no earlier than 12 months after study entry. Over the three year follow up period, approximately 75% of the ILUVIEN treated subjects received only one ILUVIEN implant.

The most common ocular (study eye) and non-ocular adverse reactions are shown in Tables 1 and 2:

Table 1: Ocular Adverse Reactions Reported by ≥1% of DME Patients and Non-ocular Adverse Reactions Reported by ≥5% of DME Patients
Adverse Reactions | ILUVIEN (N=375) n (%) | Sham (N=185) n (%)
Ocular
Cataract^1 | 192/235^2 (82%) | 61/121^2 (50%)
Myodesopsia | 80 (21%) | 17 (9%)
Eye pain | 57 (15%) | 25 (14%)
Conjunctival haemorrhage | 50 (13%) | 21 (11%)
Posterior capsule opacification | 35 (9%) | 6 (3%)
Eye irritation | 30 (8%) | 11 (6%)
Vitreous detachment | 26 (7%) | 12 (7%)
Conjunctivitis | 14 (4%) | 5 (3%)
Corneal oedema | 13 (4%) | 3 (2%)
Foreign body sensation in eyes | 12 (3%) | 4 (2%)
Eye pruritus | 10 (3%) | 3 (2%)
Ocular hyperaemia | 10 (3%) | 3 (2%)
Optic atrophy | 9 (2%) | 2 (1%)
Ocular discomfort | 8 (2%) | 1 (1%)
Photophobia | 7 (2%) | 2 (1%)
Retinal exudates | 7 (2%) | 0 (0%)
Anterior chamber cell | 6 (2%) | 1 (1%)
Eye discharge | 6 (2%) | 1 (1%)
Non-ocular
Anemia | 40 (11%) | 10 (5%)
Headache | 33 (9%) | 11 (6%)
Renal Failure | 32 (9%) | 10 (5%)
Pneumonia | 28 (7%) | 8 (4%)
^1 Includes cataract, cataract nuclear, cataract subcapsular, cataract cortical and cataract diabetic in patients who were phakic at baseline. Among these patients, 80% of ILUVIEN subjects vs. 27% of sham-controlled subjects underwent cataract surgery.
^2 235 of the 375 ILUVIEN subjects were phakic at baseline; 121 of 185 sham-controlled subjects were phakic at baseline.

Increased Intraocular Pressure (IOP) in DME Patients

Table 2: Summary of Elevated IOP Related Adverse Reactions in DME Patients
Event | ILUVIEN (N=375) n (%) | Sham (N=185) n (%)
IOP elevation ≥ 10 mmHg from Baseline | 127 (34%) | 18 (10%)
IOP elevation ≥ 30 mmHg | 75 (20%) | 8 (4%)
Any IOP-lowering medication | 144 (38%) | 26 (14%)
Any surgical intervention for elevated intraocular pressure | 18 (5%) | 1 (1%)

Figure 1: Mean IOP in DME Patients

Cataracts and Cataract Surgery in DME Patients
In the DME studies at baseline, 235 of the 375 ILUVIEN subjects were phakic; 121 of 185 sham-controlled subjects were phakic. The incidence of cataract development in patients who had a phakic study eye was higher in the ILUVIEN group (82%) compared with Sham (50%). The median time of cataract being reported as an adverse event was approximately 12 months in the ILUVIEN group and 19 months in the Sham group. Among these patients, 80% of ILUVIEN subjects vs. 27% of sham-controlled subjects underwent cataract surgery, generally within the first 18 months (Median Month 15 for both ILUVIEN group and for Sham) of the studies.

Chronic Non-Infectious Uveitis Affecting the Posterior Segment of the Eye

Studies 1 and 2 were multicenter, randomized, sham injection-controlled, double-masked trials in which patients with non-infectious uveitis affecting the posterior segment of the eye were treated once with either fluocinolone acetonide intravitreal implant or sham injection, and then received standard care for the duration of the study. Study 3 was a multicenter, randomized, masked trial in which patients with non-infectious uveitis affecting the posterior segment of the eye were all treated once with fluocinolone acetonide intravitreal implant, administered by one of two different applicators, and then received standard care for the duration of the study.

Table 3 summarizes data available from studies 1, 2 and 3 through 12 months for study eyes treated with fluocinolone acetonide intravitreal implant (n=226) or sham injection (n=94). The most common ocular (study eye) and non-ocular adverse reactions in patients with non-infectious uveitis are shown in Table 3 and Table 4.

Table 3: Ocular Adverse Reactions Reported in ≥ 1% of Subject Eyes and Non-Ocular Adverse Reactions Reported in ≥ 2% of Patients with Non-Infectious Uveitis
Ocular
ADVERSE REACTIONS | Fluocinolone acetonide intravitreal implant (N=226 Eyes) n (%) | Sham Injection (N=94 Eyes) n (%)
Cataract^1 | 63/113 (56%) | 13/56 (23%)
Visual Acuity Reduced | 33 (15%) | 11 (12%)
Macular Edema | 25 (11%) | 33 (35%)
Uveitis | 22 (10%) | 33 (35%)
Conjunctival Hemorrhage | 17 (8%) | 5 (5%)
Eye Pain | 17 (8%) | 12 (13%)
Hypotony Of Eye | 16 (7%) | 1 (1%)
Anterior Chamber Inflammation | 12 (5%) | 6 (6%)
Dry Eye | 10 (4%) | 3 (3%)
Vitreous Opacities | 9 (4%) | 8 (9%)
Conjunctivitis | 9 (4%) | 5 (5%)
Posterior Capsule Opacification | 8 (4%) | 3 (3%)
Ocular Hyperemia | 8 (4%) | 7 (7%)
Vitreous Haze | 7 (3%) | 4 (4%)
Foreign Body Sensation In Eyes | 7 (3%) | 2 (2%)
Vitritis | 6 (3%) | 8 (9%)
Vitreous Floaters | 6 (3%) | 5 (5%)
Eye Pruritus | 6 (3%) | 5 (5%)
Conjunctival Hyperemia | 5 (2%) | 2 (2%)
Ocular Discomfort | 5 (2%) | 1 (1%)
Macular Fibrosis | 5 (2%) | 2 (2%)
Glaucoma | 4 (2%) | 1 (1%)
Photopsia | 4 (2%) | 2 (2%)
Vitreous Hemorrhage | 4 (2%) | 0
Iridocyclitis | 3 (1%) | 7 (7%)
Eye Inflammation | 3 (1%) | 2 (2%)
Choroiditis | 3 (1%) | 1 (1%)
Eye Irritation | 3 (1%) | 1 (1%)
Visual Field Defect | 3 (1%) | 0
Lacrimation Increased | 3 (1%) | 0
Non-ocular
ADVERSE REACTIONS | Fluocinolone acetonide intravitreal implant (N=214 Patients) n (%) | Sham Injection (N=94 Patients) n (%)
Nasopharyngitis | 10 (5%) | 5 (5%)
Hypertension | 6 (3%) | 1 (1%)
Arthralgia | 5 (2%) | 1 (1%)
^1 Includes cataract, cataract subcapsular and lenticular opacities in study eyes that were phakic at baseline. 113 of the 226 fluocinolone acetonide study eyes were phakic at baseline; 56 of 94 sham-controlled study eyes were phakic at baseline.

Table 4: Summary of Elevated IOP Related Adverse Reactions in Patients with Non-Infectious Uveitis
ADVERSE REACTIONS | Fluocinolone acetonide intravitreal implant (N=226 Eyes) n (%) | Sham (N=94 Eyes) n (%)
IOP elevation ≥ 10 mmHg from Baseline | 50 (22%) | 11 (12%)
IOP elevation > 30 mmHg | 28 (12%) | 3 (3%)
Any IOP-lowering medication | 98 (43%) | 39 (41%)
Any surgical intervention for elevated IOP | 5 (2%) | 2 (2%)

Figure 2: Mean IOP in Patients with Non-Infectious Uveitis

6.2 Postmarketing Experience

The following adverse reactions have been identified during postapproval use of ILUVIEN. Because these reactions are reported voluntarily from a population of uncertain size, it is not always possible to estimate their frequency or establish a causal relationship to drug exposure. These reactions include reports of drug administration error and reports of the drug being ineffective.

8 USE IN SPECIFIC POPULATIONS

8.1 Pregnancy

Risk Summary

There are no adequate and well-controlled studies of ILUVIEN use in pregnant women to inform a drug-associated risk. Animal reproduction studies have not been conducted with fluocinolone acetonide. Corticosteroids have been shown to be teratogenic in laboratory animals when administered systemically at relatively low dosage levels. It is not known whether ILUVIEN can cause fetal harm when administered to a pregnant women or affect reproduction capacity. ILUVIEN should be used during pregnancy only if the potential benefit justifies the potential risk to the fetus.

All pregnancies have a background risk of birth defect, loss, or other adverse outcomes. In the United States general population, the estimated background risk of major birth defects and miscarriage in clinically recognized pregnancies is 2% to 4% and 15% to 20%, respectively.

8.2 Lactation

Risk Summary

Systemically administered corticosteroids that are present in human milk can suppress growth and interfere with endogenous corticosteroid production. Clinical or nonclinical lactation studies have not been conducted with ILUVIEN. The systemic concentration of fluocinolone acetonide following intravitreal treatment with ILUVIEN is low [see Clinical Pharmacology (12.3)].
It is not known whether intravitreal treatment with ILUVIEN could result in sufficient systemic absorption to produce detectable quantities in human milk, or affect breastfed infants or milk production. Exercise caution when ILUVIEN is administered to a nursing woman.
The developmental and health benefits of breastfeeding should be considered, along with the mother’s clinical need for ILUVIEN and any potential adverse effects on the breastfed infant from ILUVIEN or from the underlying maternal condition.

8.4 Pediatric Use

The safety and effectiveness of ILUVIEN have not been established in pediatric patients.

8.5 Geriatric Use

No overall differences in safety or effectiveness have been observed between elderly and younger patients.

11 DESCRIPTION

ILUVIEN is a sterile non-bioerodable intravitreal implant containing 0.19 mg (190 mcg) fluocinolone acetonide in a 36-month sustained-release drug delivery system. ILUVIEN is designed to release fluocinolone acetonide at an initial rate of 0.25 mcg/day. ILUVIEN is preloaded into a single-use applicator to facilitate injection of the implant directly into the vitreous. The drug substance is a synthetic corticosteroid, fluocinolone acetonide.

The chemical name for fluocinolone acetonide is (6α,11β, 16α)-6,9-difluoro-11,21-dihydroxy-16,17-[(1-methylethylidene)bis-(oxy)]-pregna-1,4-diene-3,20-dione. Its chemical structure is:

MW 452.50; molecular formula C24H30F206

Fluocinolone acetonide is a white or almost white, microcrystalline powder, practically insoluble in water, soluble in methanol, ethanol, chloroform and acetone, and sparingly soluble in ether.

Each ILUVIEN consists of a light brown 3.5mm x 0.37mm implant containing 0.19 mg of the active ingredient fluocinolone acetonide and the following inactive ingredients: polyimide tube, polyvinyl alcohol, silicone adhesive and water for injection.

12 CLINICAL PHARMACOLOGY

12.1 Mechanism of Action

Corticosteroids inhibit inflammatory responses to a variety of inciting agents including multiple inflammatory cytokines. They inhibit edema, fibrin deposition, capillary dilation, leukocyte migration, capillary proliferation, fibroblast proliferation, deposition of collagen, and scar formation associated with inflammation.

Corticosteroids are thought to act by inhibition of phospholipase A2 via induction of inhibitory proteins collectively called lipocortins. It is postulated that these proteins control biosynthesis of potent mediators of inflammation such as prostaglandins and leukotrienes by inhibiting release of the common precursor, arachidonic acid. Arachidonic acid is released from membrane phospholipids by phospholipase A2.

12.3 Pharmacokinetics

In a human pharmacokinetic study of ILUVIEN, fluocinolone acetonide concentrations in plasma were below the lower limit of quantitation of the assay (100 pg/mL) at all post-administration time points from Day 7 through Month 36 following intravitreal administration of a 0.2 mcg/day or 0.5 mcg/day fluocinolone acetonide insert.

13 NONCLINICAL TOXICOLOGY

13.1 Carcinogenesis, Mutagenesis, Impairment of Fertility

Long-term animal studies have not been conducted to determine the carcinogenic potential or the effect on fertility of ILUVIEN.

Fluocinolone acetonide was not genotoxic in vitro in the Ames test (S. typhimurium and E. coli) and the mouse lymphoma TK assay, or in vivo in the mouse bone marrow micronucleus assay.

14 CLINICAL STUDIES

Diabetic Macular Edema

The efficacy of ILUVIEN was assessed in two three year, randomized (2:1, active: sham), multicenter, double-masked, parallel-groups studies that enrolled patients with diabetic macular edema (DME) that had previously been treated with laser photocoagulation.

The primary efficacy endpoint in both trials was the proportion of subjects in whom vision had improved by 15 letters or more from baseline after 24 months of follow-up.

Table 5: Baseline BCVA (Letters)
 | Study 1 |  | Study 2
 | ILUVIEN (N=190) | Sham (N=95) | ILUVIEN (N=186) | Sham (N=90)
Mean (SD) Median (Range) | 53 (13) 57 (19-75) | 55 (11) 58 (25-69) | 53 (12) 56 (20-70) | 55 (11) 58 (21-68)

Table 6: Visual Acuity Outcomes at Month 24 (All randomized subjects with LOCF)
Study | Outcomes | ILUVIEN | Sham | Estimated Difference (95% CI)
1a | Gain of ≥15 letters in BCVA (n (%)) | 51 (27%) | 14 (15%) | 12.1% (2.6%, 21.6%)
1a | Loss of ≥15 letters in BCVA (n (%)) | 26 (14%) | 5 (5%) | 8.4% (1.8%, 15.1%)
1a | Mean change from baseline in BCVA (SD) | 3.7 (18.7) | 3.2 (13.1) | 1.8 (-2.8, 6.3)
2b | Gain of ≥15 letters in BCVA (n (%)) | 57 (31%) | 16 (18%) | 13.0% (2.7%, 23.4%)
2b | Loss of ≥15 letters in BCVA (n (%)) | 22 (12%) | 9 (10%) | 1.8% (-5.9%, 9.6%)
2b | Mean change from baseline in BCVA (SD) | 5.2 (18.0) | 0.0 (15.6) | 6.1 (1.4, 10.8)
aStudy 1: ILUVIEN, N=190; Sham, N=95
bStudy 2: ILUVIEN, N=186; Sham, N=90

Visual acuity outcomes by lens status (Phakic or Pseudophakic) at different visits are presented in Figure 3 and Figure 4. The occurrence of cataracts impacted visual acuity during the study. Patients who were pseudophakic at baseline achieved greater mean BCVA change from baseline at the Month 24 study visit.

Figure 3: Proportion of Subjects with >=15 Letters Improvement from Baseline BCVA in the Study Eye

Figure 4: Mean BCVA Change from Baseline

The BCVA outcomes for the Pseudophakic and Phakic subgroups from Studies 1 and 2 at Month 24 are presented in Table 7.

Table 7: Visual Acuity outcomes at Month 24 (Subgroup for pooled data with LOCF)
Lens Status | Outcomes | ILUVIEN | Sham | Estimated Difference (95% CI)
aPseudophakic | Gain of ≥15 letters in BCVA (n (%)) | 39 (28%) | 8 (13%) | 15.4% (4.4%, 26.3%)
aPseudophakic | Loss of ≥15 letters in BCVA (n (%)) | 7 (5%) | 7 (11%) | -5.9% (-14.4%, 2.5%)
aPseudophakic | Mean change from baseline in BCVA (SD) | 7.1 (14.5) | 1.5 (17.4) | 5.6 (0.7, 10.6)
bPhakic | Gain of ≥15 letters in BCVA (n (%)) | 69 (29%) | 22 (18%) | 11.1% (2.1%, 20.1%)
bPhakic | Loss of ≥15 letters in BCVA (n (%)) | 41 (17%) | 7 (6%) | 11.6% (5.2%, 18%)
bPhakic | Mean change from baseline in BCVA (SD) | 2.8 (20.1) | 1.8 (12.6) | 1 (-2.5 ,4.4)
aPseudophakic : ILUVIEN, N=140; Sham, N=64
bPhakic: ILUVIEN, N=236; Sham, N=121

Chronic Non-Infectious Uveitis Affecting the Posterior Segment

The efficacy of fluocinolone acetonide intravitreal implant was assessed in two randomized (2:1, fluocinolone acetonide intravitreal implant: sham-injection), multi-center, double-masked, parallel-groups studies (NCT #01694186 and #02746991) that enrolled patients with non-infectious uveitis affecting the posterior segment of the eye. The primary efficacy endpoint in both trials was the proportion of patients who experienced a recurrence of uveitis in the study eye within 6 months of follow-up; recurrence was also assessed at 12 months. Recurrence of uveitis was defined as either deterioration in visual acuity, vitreous haze attributable to non-infectious uveitis or the need for rescue medications.

Table 8: Efficacy Results of Recurrence of Uveitis in Randomized Study Eyes
 | Study 1 |  | Study 2
 | FAc Implant | Sham | FAc Implant | Sham
 | N = 87 | N = 42 | N = 101 | N = 52
Eyes with recurrence within 6 months, n (%) | 16 (18%) | 33 (79%) | 22 (22%) | 28 (54%)
Difference (95% CI) in recurrence rates | 60% (41%, 73%) |  | 32% (15%, 48%)
P-value | < 0.01 |  | < 0.01
Eyes with recurrence within 12 months, n (%) | 24 (28%) | 36 (86%) | 33 (33%) | 31 (60%)
Difference (95% CI) in recurrence rates | 58% (40%, 70%) |  | 27% (9%, 43%)

Figure 5: Time to First Recurrence of Uveitis (ITT: All Randomized Patients)

16 HOW SUPPLIED/STORAGE AND HANDLING

ILUVIEN® (fluocinolone acetonide intravitreal implant) 0.19 mg is supplied in a sterile, single-use preloaded applicator with a 25-gauge needle, packaged in a tray sealed with a lid inside a carton.

NDC 68611-190-02

STORAGE AND HANDLING

Storage: Store at 15°C to 30°C (59°F to 86° F).

17 PATIENT COUNSELING INFORMATION

Steroid-related Effects
Advise patients that a cataract may occur after treatment with ILUVIEN. If this occurs, advise patients that their vision will decrease, and they will need an operation to remove the cataract and restore their vision.

Advise patients that they may develop increased intraocular pressure with ILUVIEN treatment, and the increased IOP may need to be managed with eye drops, or surgery.

When to Seek Physician Advice
Advise patients that in the days following intravitreal injection of ILUVIEN, patients are at risk for potential complications including in particular, but not limited to, the development of endophthalmitis or elevated intraocular pressure.
Advise patients that if the eye becomes red, sensitive to light, painful, or develops a change in vision, they should seek immediate care from an ophthalmologist.

Driving and Using Machines
Inform patients that they may experience temporary blurred vision after injection of the implant. Advise patients not to drive or use machines until this has been resolved.

Manufactured for:
Alimera Sciences, Inc.
Baudette, MN 56623

Patented.

alimera

Package Label - Principal Display Panel – Carton

Package Label - Principal Display Panel – Lid

Package Label - Principal Display Panel – Inserter